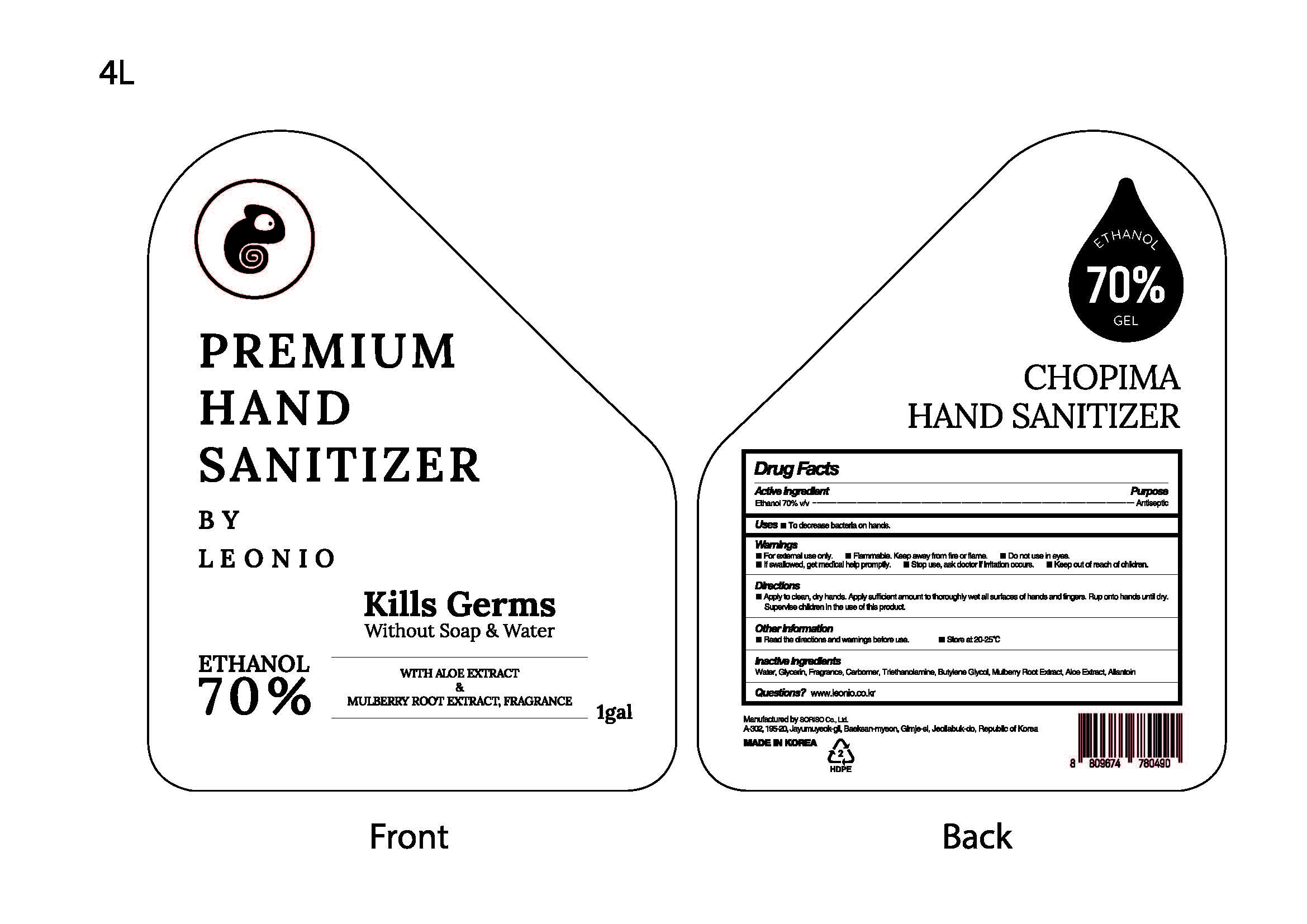 DRUG LABEL: CHOPIMA HAND SANITIZER
NDC: 69969-602 | Form: GEL
Manufacturer: Soriso
Category: otc | Type: HUMAN OTC DRUG LABEL
Date: 20200804

ACTIVE INGREDIENTS: ALCOHOL 70 mL/100 mL
INACTIVE INGREDIENTS: GLYCERIN; CARBOMER HOMOPOLYMER, UNSPECIFIED TYPE; WATER; TROLAMINE

PACKAGE LABEL

ACTIVE INGREDIENT

Alcohol

DOSAGE AND ADMINISTRATION

For external only

PURPOSE

Antiseptic

INDICATIONS AND USAGE

Apply to clean, dry hands. Apply sufficient amount to thoroughly wet all surfaces of hands and fingers. Rub onto hands until dry.

Supervise children in the use of this product.

INACTIVE INGREDIENT

Water

Glycerin

Butylene Glycol

Carbomer
Triethanolamine

Mulberry Root Extract

Aloe Extract

Allantoin

Fragrance

KEEP OUT OF REACH OF CHILDREN

WARNINGS

For external use only.

Flammable. Keep away from fire or flame.

Do not use in eyes.

If swallowed, get medical help promptly.

Stop use, ask doctor if irritation occurs.

Keep out of reach of children.